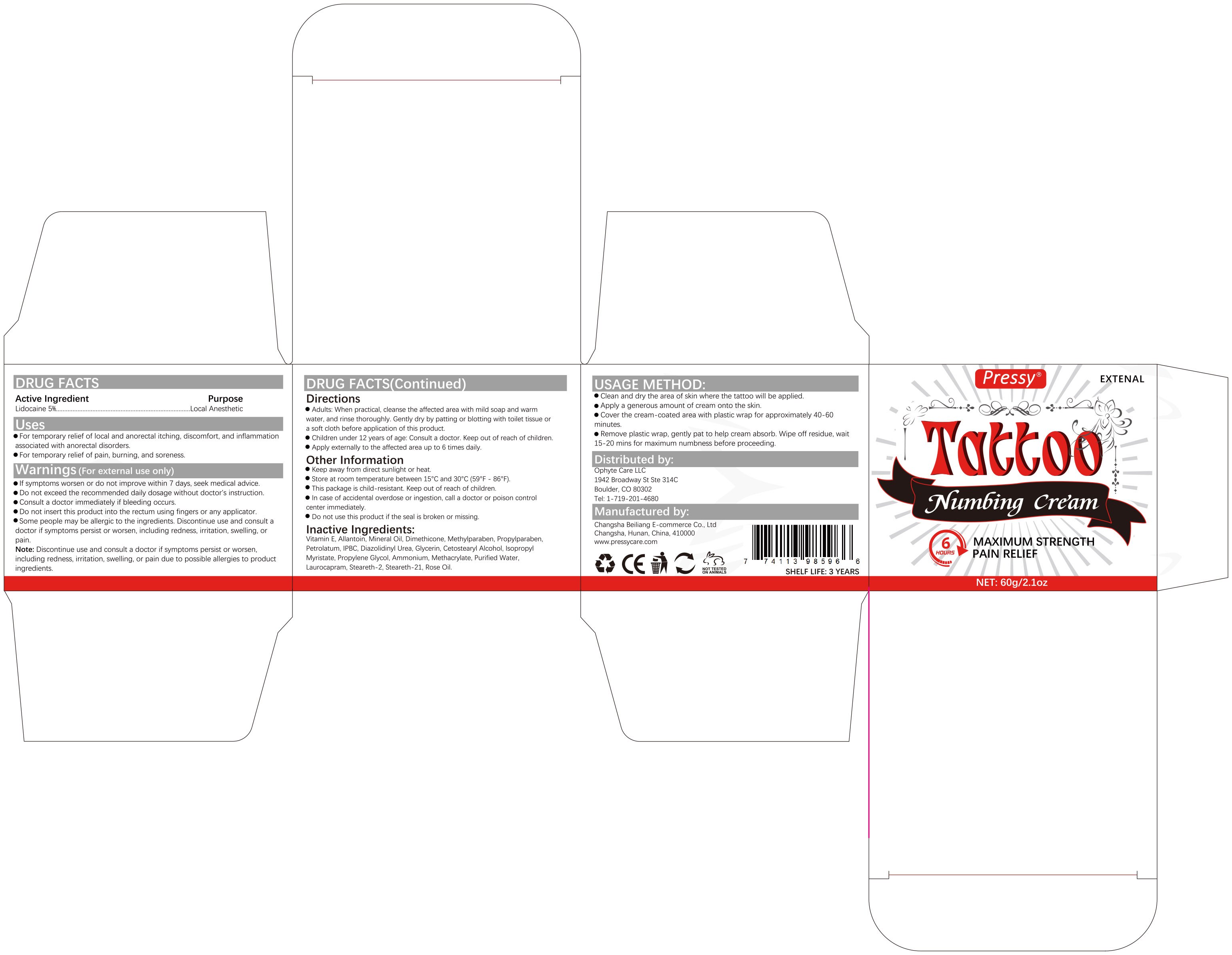 DRUG LABEL: Pressy Tattoo Numbing Cream
NDC: 83887-008 | Form: CREAM
Manufacturer: Changsha Beiliang E-commerce Co., Ltd
Category: otc | Type: HUMAN OTC DRUG LABEL
Date: 20250617

ACTIVE INGREDIENTS: LIDOCAINE 5 g/100 g
INACTIVE INGREDIENTS: DIMETHICONE; STEARETH-21; METHYLPARABEN; MINERAL OIL; PETROLATUM; PROPYLENE GLYCOL; STEARETH-2; IODOPROPYNYL BUTYLCARBAMATE; GLYCERIN; WATER; PROPYLPARABEN; DIAZOLIDINYL UREA; CETOSTEARYL ALCOHOL; LAUROCAPRAM; ALLANTOIN; AMMONIUM METHACRYLATE; ISOPROPYL MYRISTATE; ROSE OIL; .ALPHA.-TOCOPHEROL

83887-008

Active Ingredient

Lidocaine 5%

Purpose

Local Anesthetic

Use

For temporary relief of local and anorectal itching, discomfort, and inflammation associated with anorectal disorders.
For temporary relief of pain, burning, and soreness.

Warnings

1. If symptoms worsen or do not improve within 7 days, seek medical advice.
2. Do not exceed the recommended daily dosage without a doctor's instruction.
3. Consult a doctor immediately if bleeding occurs.
4. Do not insert this product into the rectum using fingers or any applicator.
5. Some people may be allergic to the ingredients. Discontinue use and consult a doctor if symptoms persist or worsen, including redness, irritation, swelling, or pain.
Note: Discontinue use and consult a doctor if symptoms persist or worsen, including redness, irritation, swelling, or pain due to possible allergies to product ingredients.

Do not use this product if the seal is broken or missing.

When Using

If symptoms worsen or do not imorove within 7 davs
seek medicaladvice,Do not exceed the recommended daily dosage
Do not insert this product into the rectum using fingers or any applicator
Some peoole mav be aleroic to he inoredients, biscontinwe use and consut a doctor if symotoms persistor worsen including redness irtation swelina or nain
without doctor'sinstruction.Consult a doctor immediately if bleedina occurs

Stop Use

Discontinue use and consult a doctor if symptoms persist or worsen, including redness, irritation, swelling, or pain due to possible allergies to product ingredients.

Ask Doctor

Discontinue use and consul a doctor if symptoms persist or worsen, including redness, iritaion. sweling, or pain due to possible
allergies to product ingredients

Keep Out Of Reach Of Children

This package is child-resistant.Keep out of reach of children

Directions

Adults: When practical.
cleanse theaffected area with mild soap andwarm water.
and rinse thoroughlyGently dry by patting or blotting withtoilet tissue or a soft cloth beforeapplication of this product

Other information

Keep away from direct sunlight orheat
Store at room temperaturebetween 15°C to 30°C(59°F - 86°F))
This package is chld.resisiantKeep out ofreach of chidren.in case ofacidenlal overdose omgesion,cala ocororpoisonconr0. cemerimmediately. Do notuse this productifthe seals broken or mising

Inactive ingredients

Vitamin E,Allantoin,Mineral Oil,Dimethicone,Methylparaben,Propylparaben,Petrolatum,IPBC,Diazolidinyl Urea,Glycerin,Cetostearyl Alcohol,Isopropyl Myristate,Propylene Glycol,Ammonium,Methacrylate,Purified Water,Laurocapram,Steareth-2,Steareth-21,Rose Oil